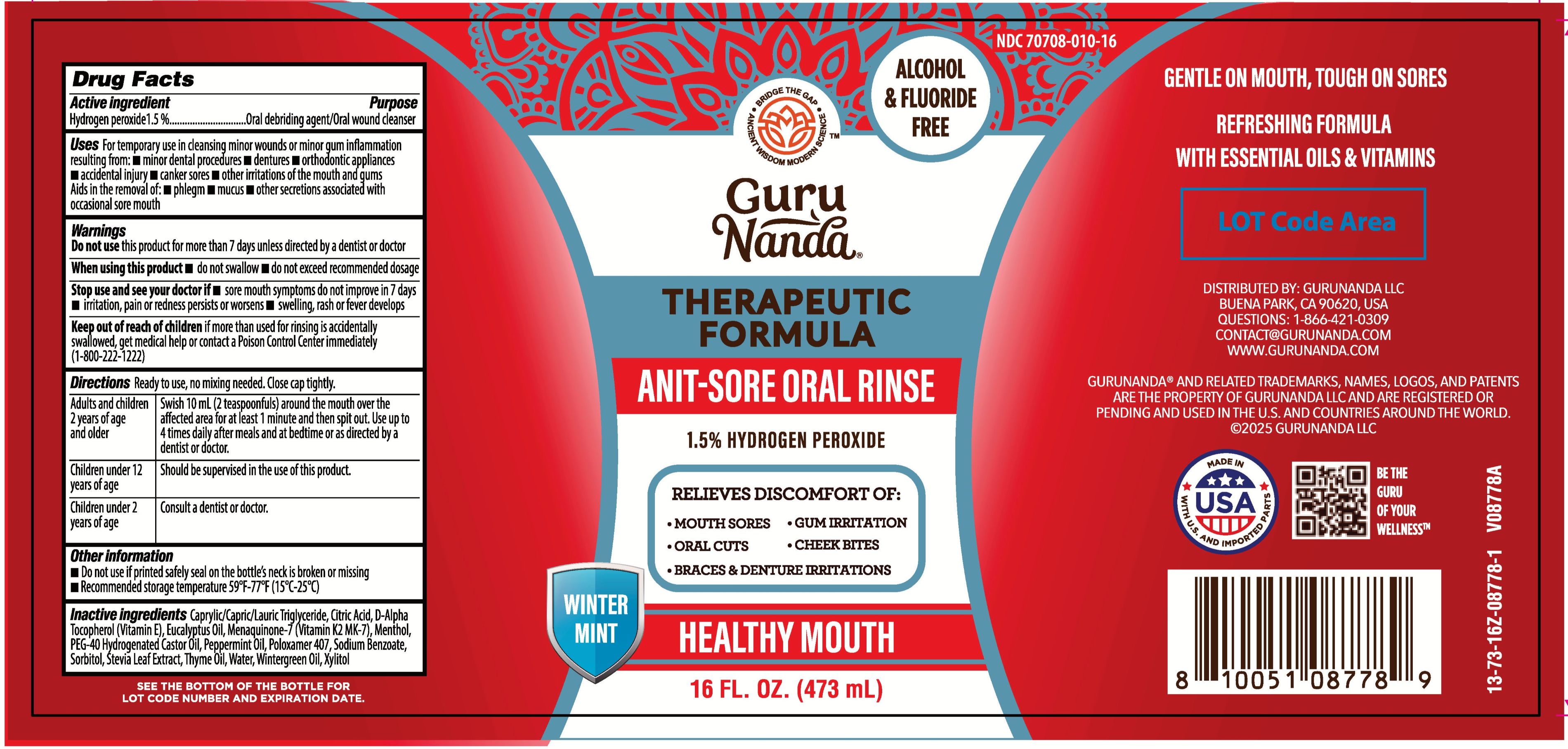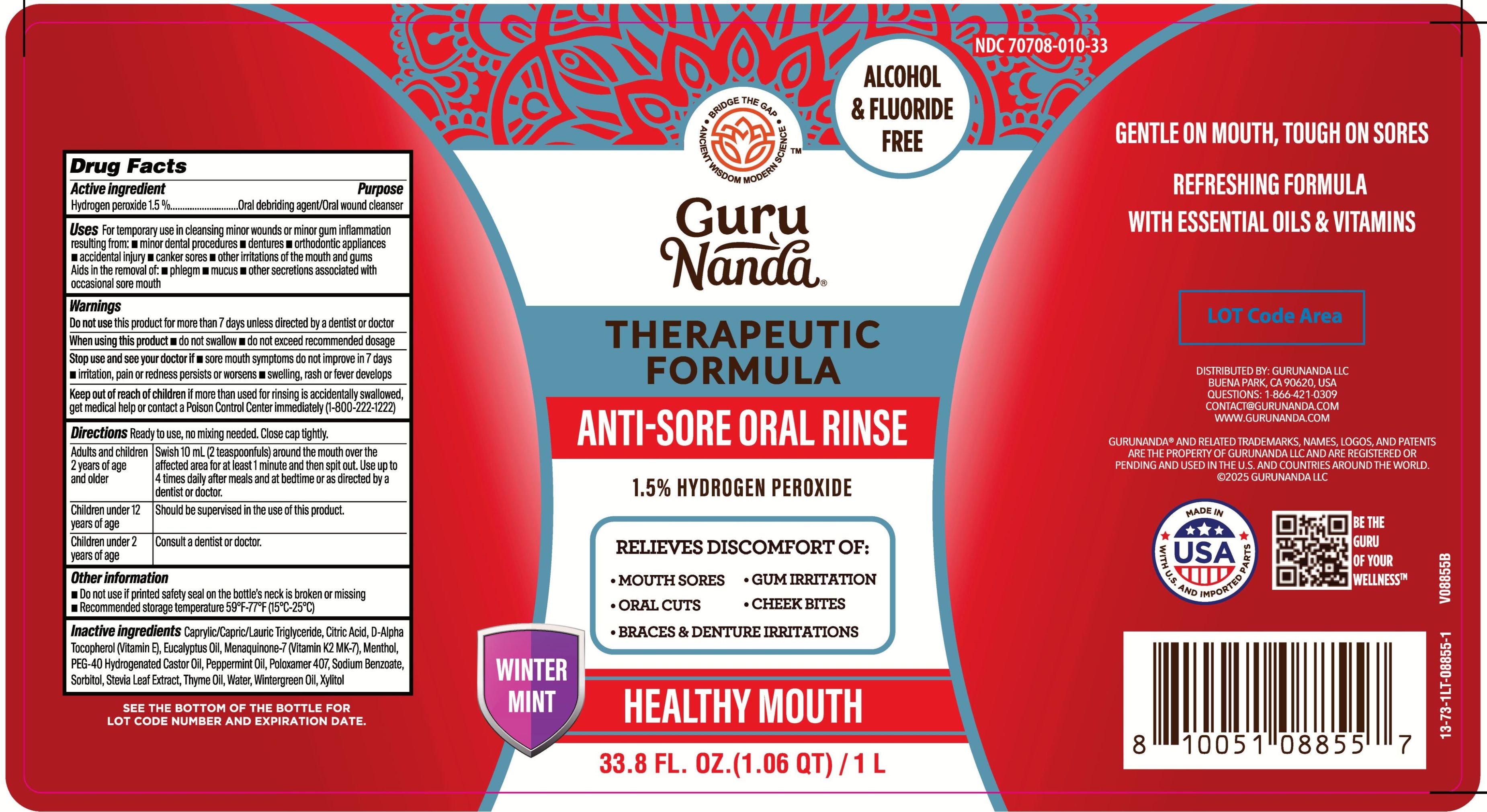 DRUG LABEL: GuruNanda Oxyfusion
NDC: 70708-010 | Form: MOUTHWASH
Manufacturer: GURUNANDA, LLC
Category: otc | Type: HUMAN OTC DRUG LABEL
Date: 20251111

ACTIVE INGREDIENTS: HYDROGEN PEROXIDE 15 mg/1 mL
INACTIVE INGREDIENTS: MENAQUINONE 7; .ALPHA.-TOCOPHEROL, D-; EUCALYPTUS OIL; MENTHA PIPERITA (PEPPERMINT) OIL; SORBITOL; WATER; POLOXAMER 407; XYLITOL; GAULTHERIA PROCUMBENS (WINTERGREEN) LEAF OIL; PEG-40 HYDROGENATED CASTOR OIL; CITRIC ACID; STEVIA REBAUDIUNA LEAF; SODIUM BENZOATE; CAPRYLIC/CAPRIC/LAURIC TRIGLYCERIDE; THYME OIL; LEVOMENTHOL

GuruNanda Anti-Sore Oral Rinse

Active ingredient

Hydrogen peroxide 1.5%

Purpose

Oral debriding agent/oral antiseptic

Uses

For temporary use in cleansing minor wounds or minor gum inflammation resulting from:

- minor dental procedures
- dentures
- orthodontic appliances
- accidental injury
- canker sores
- other irritations of the mouth and gums

Aids in the removal of:

- phlegm
- mucus
- other secretions associated with occasional sore mouth

Warnings

Do not use

this product for more than 7 days unless directed by a dentist or doctor

When using this product

- do not swallow
- do not exceed recommended dosage

Stop use and see your dotor if

- sore mouth symptoms do not improve in 7 days
- irritation, pain or redness persists or worsens
- swelling, rash or fever develops

Keep out of reach of children

if more than used for rinsing is accidently swallowed, get medical help or contact a Poison Control Center immediately (1-800-222-1222)

Directions

Ready to use, no mixxing needed. Close cap tightly.

Adults and children 2 years of age and older: Swish 10 mL around the mouth over the affected area for at least 1 minute and then spit out. Use up to 4 times daily after meals and at bedtime or as directed by a dentist or doctor.

Children under 12 years of age: Should be supervised in the use of this product.

Children under 2 years of age: Consult a dentist or doctor.

Other information

- Do not use if printed safety seal on the bottle's neck is broken or missing
- Recommended storage temperature 59°F-77°F (15°C-25°C)

Inactive ingredients

Caprylic/Capric/Lauric Triglyceride, Citric Acid, D-Alpha Tocopherol (Vitamin E), Eucalyptus Oil, Menaquinone-7 (Vitamin K2 MK-7), Menthol, PEG-40 Hydrogenated Castor Oil, Peppermint Oil, Poloxamer 407, Sodium Benzoate, Sorbitol, Stevia Leaf Extract, Thyme Oil, Water, Wintergreen, Oil, Xylitol